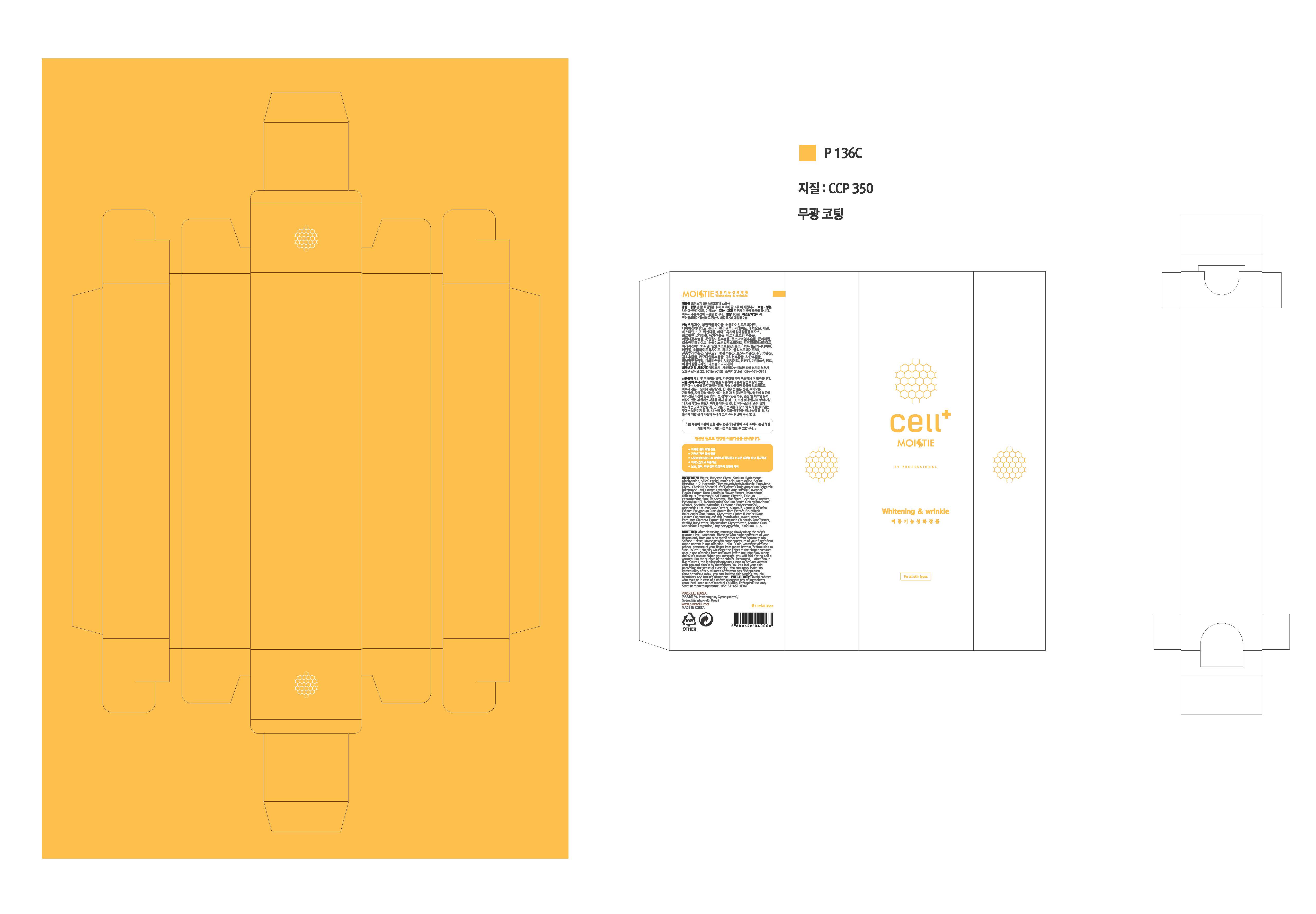 DRUG LABEL: MOISTIE CELL PLUS
NDC: 71609-0003 | Form: CREAM
Manufacturer: Purecell Korea Co., Ltd.
Category: otc | Type: HUMAN OTC DRUG LABEL
Date: 20180929

ACTIVE INGREDIENTS: NIACINAMIDE 2 g/100 mL; ADENOSINE 0.04 g/100 mL
INACTIVE INGREDIENTS: WATER; GLYCERIN; BUTYLENE GLYCOL

Drug Facts

ACTIVE INGREDIENT

Niacinamide, Adenosine

INACTIVE INGREDIENT

Water, Glycerin, Butylene Glycol

PURPOSE

Skin Protectant - Whitening & Anti-wrinkle

keep out or reach of the children

INDICATIONS AND USAGE

1. After cleansing, massage slowly along your face skin's texture. (After cleansing, You can do it after applying your skin softner)
2. Forehead
Massage with proper pressure of the finger from top to bottom in one direction.
3. Chin
Massage with proper pressure of the fingers from top to bottom, or from side to side in one direction.
4. Cheek
Massage the finger at the proper pressure only in one direction from the lower jaw to the upper jaw along the skin's texture.
5. Finish,
with lotion or cream after fever disappears. you can make up. It is usually done in the evening or at night.
6. After the heat is gone, finish with lotion or cream. It is usually done in the evening or at night. (You can use it once a week even if it is used in dermatology)

WARNINGS

1. Do not use in the following cases(Eczema and scalp wounds)
2.Side Effects
1)Due to the use of this druf if rash, irritation, itching and symptopms of hypersnesitivity occur dicontinue use and consult your phamacisr or doctor
3.General Precautions
1)If in contact with the eyes, wash out thoroughty with water If the symptoms are servere, seek medical advice immediately
2)This product is for exeternal use only. Do not use for internal use
4.Storage and handling precautions
1)If possible, avoid direct sunlight and store in cool and area of low humidity
2)In order to maintain the quality of the product and avoid misuse
3)Avoid placing the product near fire and store out in reach of children

DOSAGE AND ADMINISTRATION

for external use only